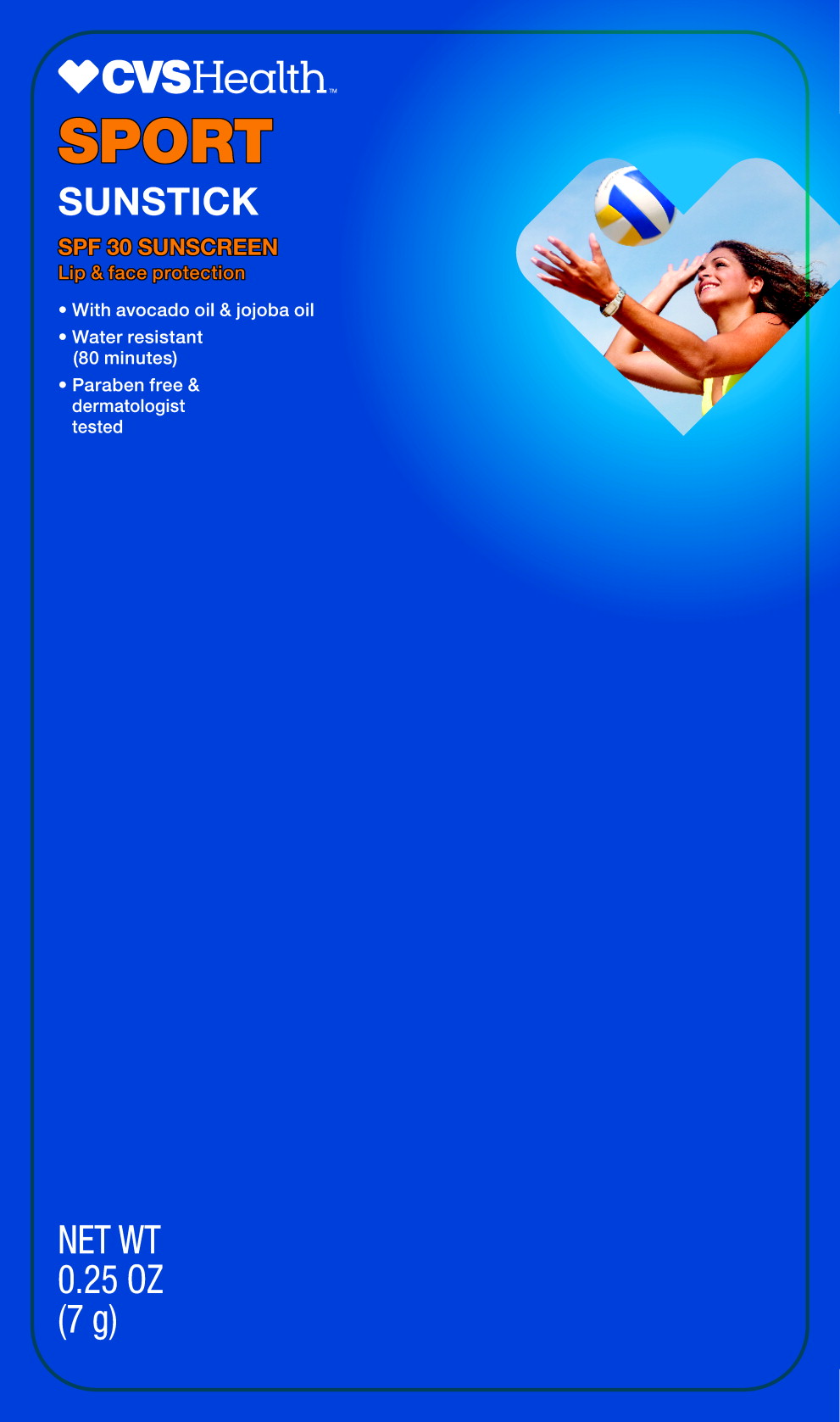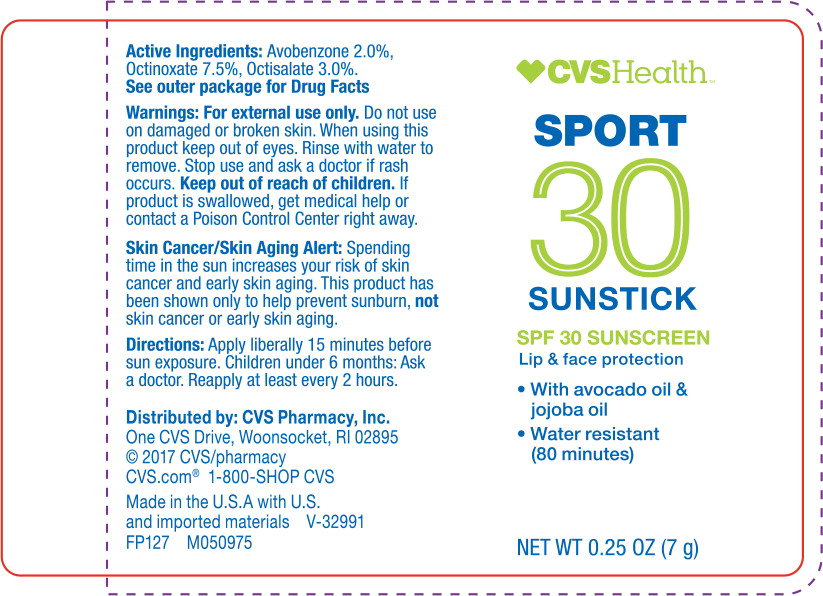 DRUG LABEL: Sport Sunstick SPF 30 Sunscreen
NDC: 69842-083 | Form: STICK
Manufacturer: CVS Health
Category: otc | Type: HUMAN OTC DRUG LABEL
Date: 20170417

ACTIVE INGREDIENTS: avobenzone 20 mg/1 g; octinoxate 75 mg/1 g; octisalate 30 mg/1 g
INACTIVE INGREDIENTS: WHITE WAX; RICINUS COMMUNIS SEED; HYDROGENATED OLIVE OIL DECYL ESTERS; JOJOBA OIL; GRAPE SEED OIL; CARNAUBA WAX; AVOCADO OIL; MEADOWFOAM SEED OIL; PASSIFLORA INCARNATA SEED OIL; SUCROSE TETRASTEARATE TRIACETATE; LEMON OIL; RIBES NIGRUM SEED OIL; TOCOPHEROL; ASCORBYL TETRAISOPALMITATE; ASCORBYL PALMITATE; AMMONIUM GLYCYRRHIZATE; BUTYLATED HYDROXYTOLUENE; PHENOXYETHANOL

Drug Facts

Active ingredients

Avobenzone 2.0%

Octinoxate 7.5%

Octisalate 3.0%

Purpose

Sunscreen

Sunscreen

Sunscreen

Uses

Helps prevent sunburn

Warnings

For external use only.

Do not use on damaged or broken skin

Stop use and ask a doctor if rash occurs.

When using this product keep out of eyes. Rinse with water to remove.

Keep out of reach of children. If swallowed, get medical help or contact a Poison Control Center right away.

Skin Cancer/Skin Aging Alert: Spending time in the sun increases your risk of skin cancer and early skin aging. This product has been shown only to help prevent sunburn, not skin cancer or early skin aging.

Directions

- Apply liberally 15 minutes before sun exposure
- children under the age of 6: Ask a doctor
- reapply at least every 2 hours
- reapply after 80 minutes of swimming or sweating and immediately after towel drying

Other information

- Protect the product in this container from excessive heat and direct sunlight.

Inactive ingredients

Cera Alba, Ricinus Communis, Hydrogenated Olive Oil Decyl Esters, Simmondsia Chinensis (Jojoba) Seed Oil, Vitis Vinifera (Grape) Seed Oil, Copernicia Cerifera, Fragrance, Persea Gratissima, Limnanthes Alba (Meadowfoam) Seed Oil, Passiflora Incarnata Seed Oil, Sucrose Tetrastearate Triacetate, Citrus Limon (Lemon) Peel Oil, Ribes Nigrum (Black Currant) Seed Oil, Tocopherol, Tetraisopalmitate, Ascorbyl Palmitate, Ammonium Glycyrrhizate, BHT, Phenoxyethanol

Distributed by: CVS Pharmacy, Inc.
One CVS Drive, Woonsocket, RI 02895
© 2017 CVS/pharmacy
CVS.com® 1-800-SHOP CVS

Made in the U.S.A. of U.S. and imported components
FP127 M050976 V-32991

CVS® Quality
Money Back Guarantee

Principal Display Panel - Sport Sunstick Blister Pack Label

CVS Health™

SPORT

SUNSTICK

SPF 30 SUNSCREEN

Lip & face protection

- With avocado oil & jojoba oil
- Water resistant (80 minutes)
- Paraben free & dermatologist tested

NET WT

0.25 OZ

(7 g)

Principal Display Panel - Sport Sunstick Label

CVS Health™

SPORT

30

SUNSTICK

SPF 30 SUNSCREEN

Lip & face protection

- With avocado oil & jojoba oil
- Water resistant (80 minutes)

NET WT 0.25 OZ (7 g)